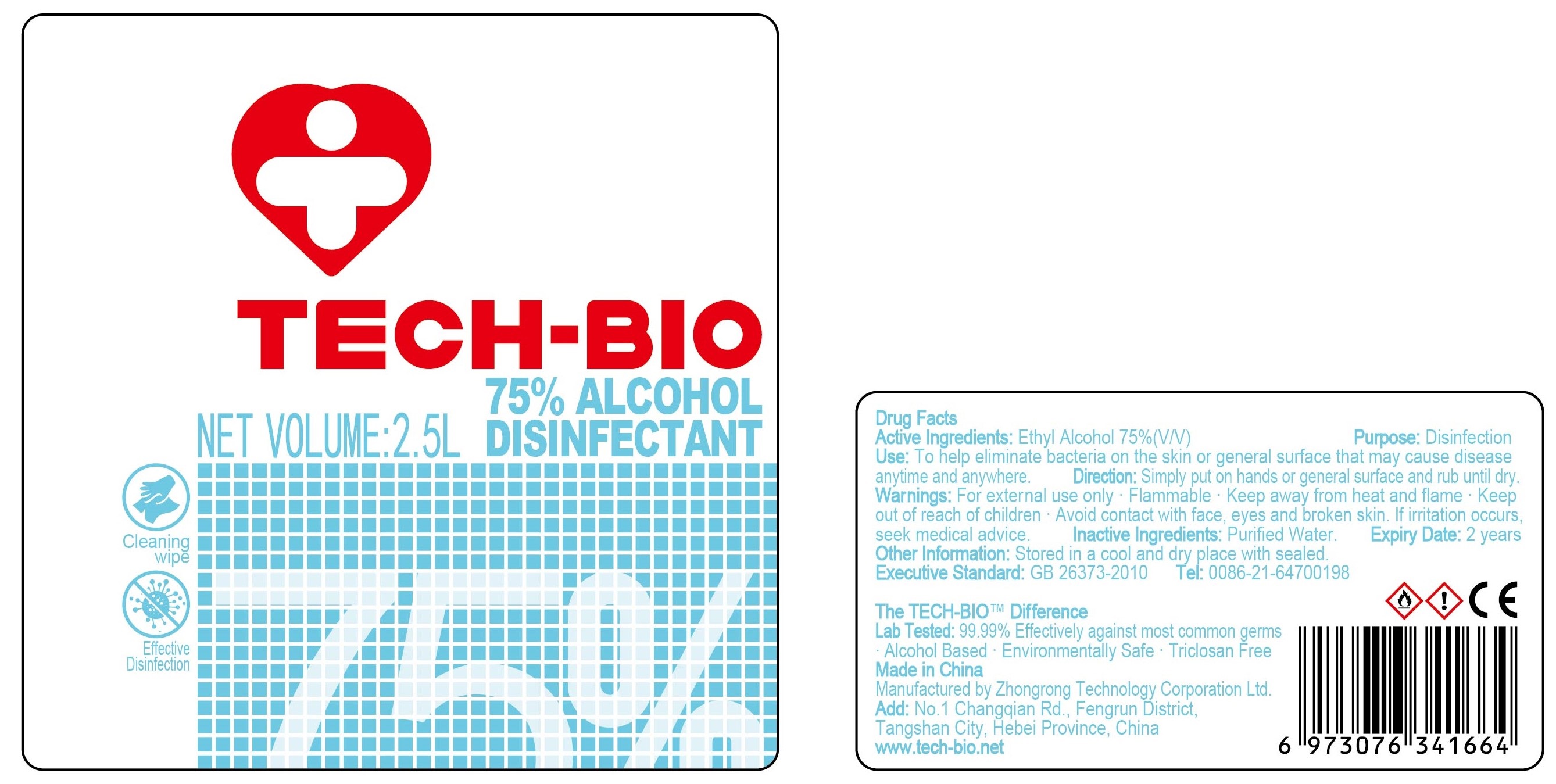 DRUG LABEL: 75% Alcohol Disinfectant
NDC: 81191-001 | Form: LIQUID
Manufacturer: Zhongrong Technology Corporation Ltd.
Category: otc | Type: HUMAN OTC DRUG LABEL
Date: 20201214

ACTIVE INGREDIENTS: ALCOHOL 75 mL/100 mL
INACTIVE INGREDIENTS: WATER

75% Alcohol Disinfectant

Active Ingredient(s)

Ethyl Alcohol 75% v/v. Purpose: Disinfection

Purpose

Disinfection, Hand Sanitizer

Use

Hand Sanitizer to help reduce bacteria that potentially can cause disease. For use when soap and water are not available.

Warnings

For external use only. Flammable. Keep away from heat and flame, Keep out of reach of children.

Avoid contact with face, eyes and broken skin. If irritation occurs, seek medical advice.

Do not use

- in children less than 2 months of age
- on open skin wounds

When using this product keep out of eyes, ears, and mouth. In case of contact with eyes, rinse eyes thoroughly with water.
Stop use and ask a doctor if irritation or rash occurs. These may be signs of a serious condition.
Keep out of reach of children. If swallowed, get medical help or contact a Poison Control Center right away.

Stop use and ask a doctor if irritation or rash occurs. These may be signs of a serious condition.

Keep out of reach of children. If swallowed, get medical help or contact a Poison Control Center right away.

Directions

- Place enough product on hands to cover all surfaces. Rub hands together until dry.
- Supervise children under 6 years of age when using this product to avoid swallowing.

Other information

- Store between 15-30C (59-86F)
- Avoid freezing and excessive heat above 40C (104F)

Inactive ingredients

purified water

Package Label - Principal Display Panel

2500 mL NDC: 81191-001-15